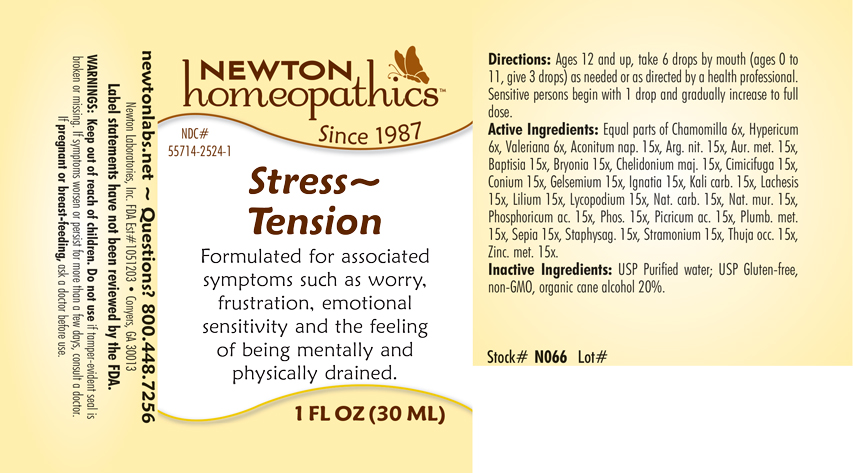 DRUG LABEL: Stress-Tension
NDC: 55714-2524 | Form: LIQUID
Manufacturer: Newton Laboratories, Inc.
Category: homeopathic | Type: HUMAN OTC DRUG LABEL
Date: 20250210

ACTIVE INGREDIENTS: MATRICARIA CHAMOMILLA 6 [hp_X]/1 mL; ACONITUM NAPELLUS 15 [hp_X]/1 mL; SILVER NITRATE 15 [hp_X]/1 mL; GOLD 15 [hp_X]/1 mL; BAPTISIA TINCTORIA ROOT 15 [hp_X]/1 mL; BRYONIA ALBA ROOT 15 [hp_X]/1 mL; CHELIDONIUM MAJUS 15 [hp_X]/1 mL; BLACK COHOSH 15 [hp_X]/1 mL; CONIUM MACULATUM FLOWERING TOP 15 [hp_X]/1 mL; GELSEMIUM SEMPERVIRENS ROOT 15 [hp_X]/1 mL; STRYCHNOS IGNATII SEED 15 [hp_X]/1 mL; POTASSIUM CARBONATE 15 [hp_X]/1 mL; LACHESIS MUTA VENOM 15 [hp_X]/1 mL; LILIUM LANCIFOLIUM WHOLE FLOWERING 15 [hp_X]/1 mL; LYCOPODIUM CLAVATUM SPORE 15 [hp_X]/1 mL; SODIUM CARBONATE 15 [hp_X]/1 mL; SODIUM CHLORIDE 15 [hp_X]/1 mL; PHOSPHORIC ACID 15 [hp_X]/1 mL; PHOSPHORUS 15 [hp_X]/1 mL; PICRIC ACID 15 [hp_X]/1 mL; LEAD 15 [hp_X]/1 mL; SEPIA OFFICINALIS JUICE 15 [hp_X]/1 mL; DELPHINIUM STAPHISAGRIA SEED 15 [hp_X]/1 mL; DATURA STRAMONIUM 15 [hp_X]/1 mL; THUJA OCCIDENTALIS LEAFY TWIG 15 [hp_X]/1 mL; HYPERICUM PERFORATUM 6 [hp_X]/1 mL; VALERIAN 6 [hp_X]/1 mL; ZINC 15 [hp_X]/1 mL
INACTIVE INGREDIENTS: ALCOHOL; WATER

Stress 2524L

DOSAGE & ADMINISTRATION SECTION

Directions: Ages 12 and up, take 6 drops by mouth (ages 0 to 11, give 3 drops) as needed or as directed by a health professional. Sensitive persons begin with 1 drop and gradually increase to full dose.

OTC - ACTIVE INGREDIENT SECTION

Equal parts of Chamomilla 6x, Hypericum perforatum 6x, Valeriana officinalis 6x, Aconitum napellus 15x, Argentum nitricum 15x, Aurum metallicum 15x, Baptisia 15x, Bryonia 15x, Chelidonium majus 15x, Cimicifuga racemosa 15x, Conium maculatum 15x, Gelsemium sempervirens 15x, Ignatia amara 15x, Kali carbonicum 15x, Lachesis mutus 15x, Lilium tigrinum 15x, Lycopodium clavatum 15x, Natrum carbonicum 15x, Natrum muriaticum 15x, Phosphoricum acidum 15x, Phosphorus 15x, Picricum acidum 15x, Plumbum metallicum 15x, Sepia 15x, Staphysagria 15x, Stramonium 15x, Thuja occidentalis 15x, Zincum metallicum 15x.

OTC - PURPOSE SECTION

Formulated for associated symptoms such as worry, frustration, emotional sensitivity and the feeling of being mentally and physically drained.

INACTIVE INGREDIENT SECTION

Inactive Ingredients: USP Purified Water; USP Gluten-free, non-GMO, organic cane alcohol 20%

QUESTIONS SECTION

newtonlabs.net - Questions? 800.448.7256

Newton Laboratories, Inc. FDA Est # 1051203 Conyers, GA 30013

WARNINGS SECTION

WARNINGS: Keep out of reach of children. Do not use if tamper-evident seal is broken or missing. If symptoms worsen or persist for more than a few days, consult a doctor. If pregnant or breast-feeding, ask a doctor before use.

OTC - PREGNANCY OR BREAST FEEDING SECTION

If pregnant or breast-feeding, ask a doctor before use.

OTC - KEEP OUT OF REACH OF CHILDREN SECTION

Keep out of reach of children.